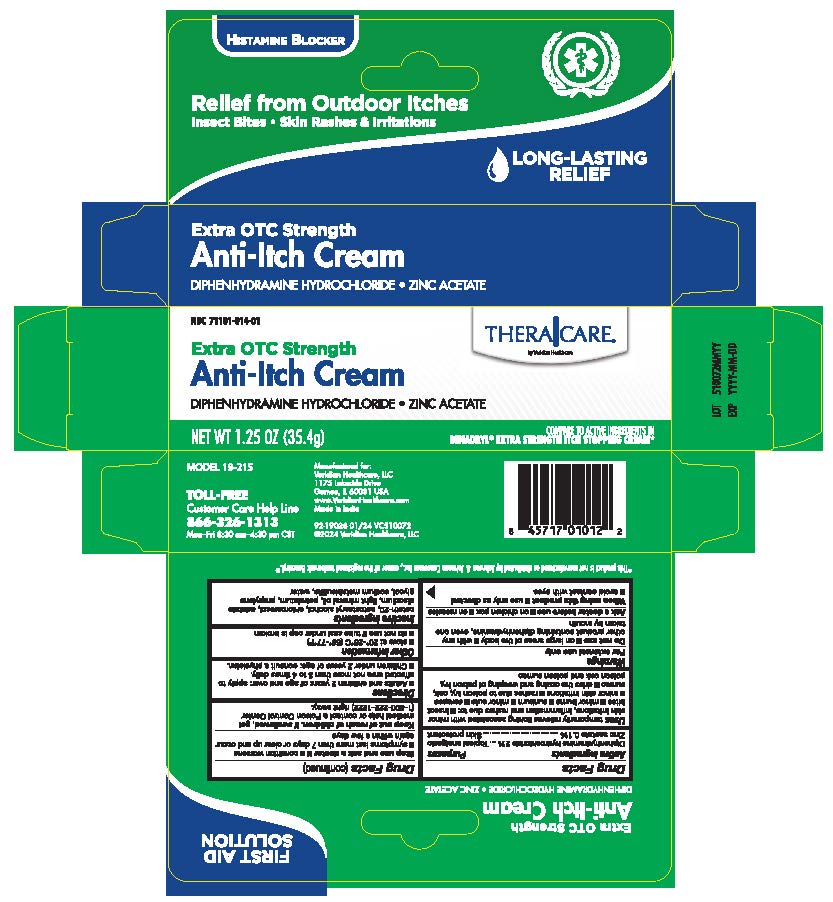 DRUG LABEL: TheraCare 2% Diphenhydramine Anti-Itch Cream
NDC: 71101-014 | Form: CREAM
Manufacturer: Veridian Healthcare
Category: otc | Type: HUMAN OTC DRUG LABEL
Date: 20251006

ACTIVE INGREDIENTS: DIPHENHYDRAMINE HYDROCHLORIDE 20 mg/1 g; ZINC ACETATE 1 mg/1 g
INACTIVE INGREDIENTS: LIGHT MINERAL OIL; CETETH-20; CETOSTEARYL ALCOHOL; PROPYLENE GLYCOL; PETROLATUM; WATER; SODIUM METABISULFITE; EDETATE DISODIUM; CHLOROCRESOL

TheraCare 2% Diphenhydramine Anti-Itch Cream

Drug Facts

ACTIVE INGREDIENT

Active ingredients | Purpose
Diphenhydramine hydrochloride 2% | Topical analgesic
Zinc acetate 0.1% | Skin protectant

Uses

- temporarily relieves pain and itching associated with:
  - insect bites
  - minor burns
  - sunburn
  - minor skin irritations
  - minor cuts
  - scrapes
  - rashes due to poison ivy, poison oak, and poison sumac
- dries the oozing and weeping of poison ivy, poison oak, and poison sumac

Warnings

For external use only.

Do not use

- on large areas of the body
- with any other product containing diphenhydramine, even one taken by mouth

Ask a doctor before use

- on chicken pox
- on measles

When using this productavoid contact with eyes

Stop use and ask a doctor if

- condition worsens or does not improve within 7 days
- symptoms persist for more than 7 days or clear up and occur again within a few days

Keep out of reach of children.If swallowed, get medical help or contact a Poison Control Center right away.

Directions

- adults and children 2 years of age and overr: apply to affected area not more than 3 to 4 times daily
- children under 2 years of age: consult a physician

Other information

- store at 20˚C-25 ˚C (68˚F-77˚F)
- do not use if tube seal under cap is broken

Inactive ingredients

ceteth-20, cetostearyl alcohol, chlorocresol, edetate disodium, light mineral oil, petrolatum, polyethylene glycol, sodium metabisulfite, water

Questions or comments?

ca ll 1-866-326-1313

Manufacturer for:

Veridian Healthcare, LLC